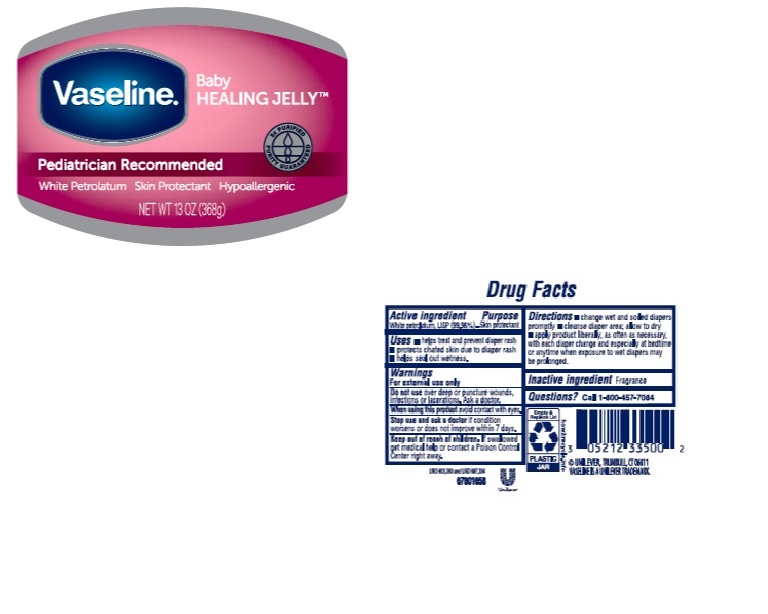 DRUG LABEL: Vaseline
NDC: 64942-1866 | Form: JELLY
Manufacturer: Conopco Inc. d/b/a Unilever
Category: otc | Type: HUMAN OTC DRUG LABEL
Date: 20250331

ACTIVE INGREDIENTS: PETROLATUM 99.96 g/100 g
INACTIVE INGREDIENTS: WATER

Vaseline Baby Healing Jelly

Active ingredient

WHITE PETROLATUM, USP (99.96%)

Purpose

skin protectant

Uses

helps treat and prevent diaper rash
protects chafed skin due to diaper rash and helps seal out wetness

Warnings

For external use only
When using this product do not get into eyes
See a doctor if condition last more than 7 days
Do not use on deep or puncture wounds, animal bites, serious burns

Keep out of reach of children
If swallowed get medical help or contact a Poison Control Center right away.

Directions

change wet and soiled diapers promptly
cleanse diaper area: allow to dry
apply product liberally, as often as necessary, with each diaper change and especially at bedtime or anytime when exposure to wet diapers may be prolonged

Inactive ingredient

Fragrance

Questions?

Call 1-800-497-7084